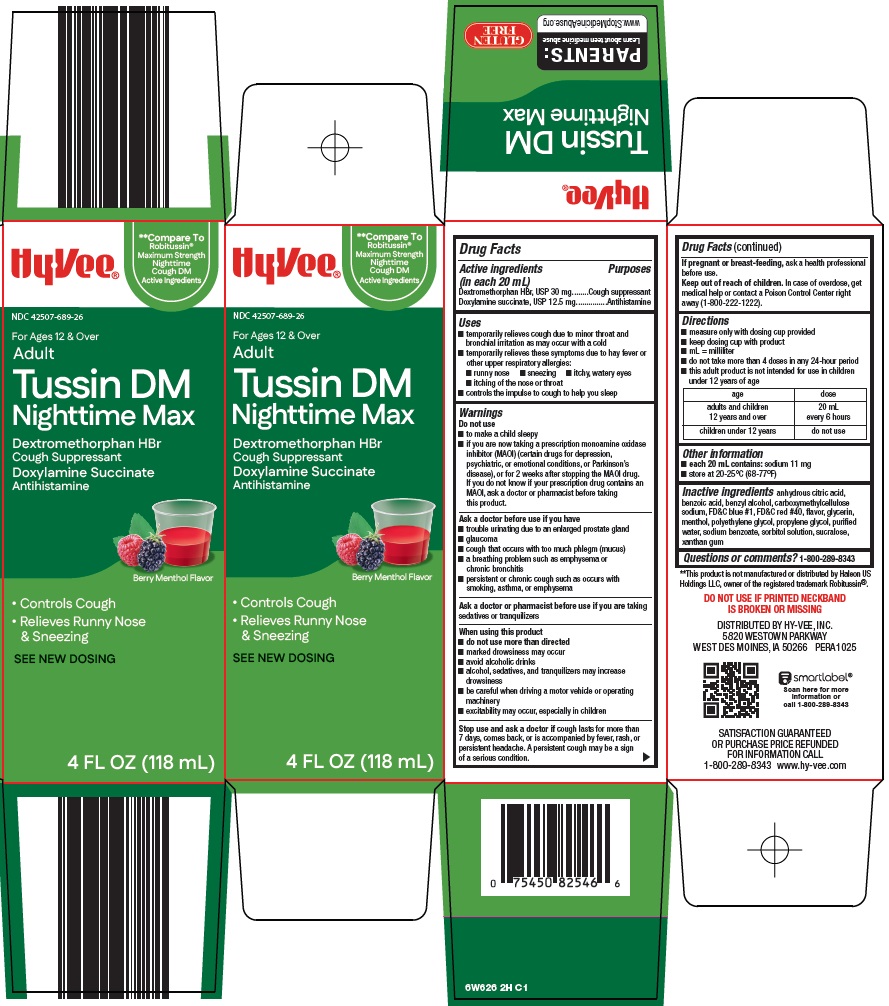 DRUG LABEL: tussin dm nighttime max
NDC: 42507-689 | Form: SOLUTION
Manufacturer: HyVee Inc
Category: otc | Type: HUMAN OTC DRUG LABEL
Date: 20260203

ACTIVE INGREDIENTS: DEXTROMETHORPHAN HYDROBROMIDE 30 mg/20 mL; DOXYLAMINE SUCCINATE 12.5 mg/20 mL
INACTIVE INGREDIENTS: ANHYDROUS CITRIC ACID; BENZOIC ACID; BENZYL ALCOHOL; CARBOXYMETHYLCELLULOSE SODIUM, UNSPECIFIED; FD&C BLUE NO. 1; FD&C RED NO. 40; GLYCERIN; MENTHOL, UNSPECIFIED FORM; POLYETHYLENE GLYCOL, UNSPECIFIED; PROPYLENE GLYCOL; WATER; SODIUM BENZOATE; SORBITOL SOLUTION; SUCRALOSE; XANTHAN GUM

Hy-Vee, Inc. Tussin DM Nighttime Max Drug Facts

Active ingredients (in each 20 mL)

Dextromethorphan HBr, USP 30 mg

Doxylamine succinate, USP 12.5 mg

Purposes

Cough suppressant

Antihistamine

Uses

- temporarily relieves cough due to minor throat and bronchial irritation as may occur with a cold
- temporarily relieves these symptoms due to hay fever or other upper respiratory allergies:
- runny nose
- sneezing
- itchy, watery eyes
- itching of the nose or throat
- controls the impulse to cough to help you sleep

Warnings

Do not use

- to make a child sleepy
- if you are now taking a prescription monoamine oxidase inhibitor (MAOI) (certain drugs for depression, psychiatric, or emotional conditions, or Parkinson's disease), or for 2 weeks after stopping the MAOI drug. If you do not know if your prescription drug contains an MAOI, ask a doctor or pharmacist before taking this product.

Ask a doctor before use if you have

- trouble urinating due to an enlarged prostate gland
- glaucoma
- cough that occurs with too much phlegm (mucus)
- a breathing problem such as emphysema or chronic bronchitis
- persistent or chronic cough such as occurs with smoking, asthma, or emphysema

Ask a doctor or pharmacist before use if you are

taking sedatives or tranquilizers

When using this product

- do not use more than directed
- marked drowsiness may occur
- avoid alcoholic drinks
- alcohol, sedatives, and tranquilizers may increase drowsiness
- be careful when driving a motor vehicle or operating machinery
- excitability may occur, especially in children

Stop use and ask a doctor if

cough lasts for more than 7 days, comes back, or is accompanied by fever, rash, or persistent headache. A persistent cough may be a sign of a serious condition.

If pregnant or breast-feeding,

ask a health professional before use.

Keep out of reach of children.

In case of overdose, get medical help or contact a Poison Control Center right away (1-800-222-1222).

Directions

- measure only with dosing cup provided
- keep dosing cup with product
- mL = milliliter
- do not take more than 4 doses in any 24-hour period
- this adult product is not intended for use in children under 12 years of age

age | dose
adults and children 12 years and over | 20 mL every 6 hours
children under 12 years | do not use

Other information

- each 20 mL contains: sodium 11 mg
- store at 20-25°C (68-77°F)

Inactive ingredients

anhydrous citric acid, benzoic acid, benzyl alcohol, carboxymethylcellulose sodium, FD&C blue #1, FD&C red #40, flavor, glycerin, menthol, polyethylene glycol, propylene glycol, purified water, sodium benzoate, sorbitol solution, sucralose, xanthan gum

Questions or comments?

1-800-289-8343

Package/Label Principal Display Panel

Hy•Vee®

Compare To Robitussin® Maximum Strength Nighttime Cough DM Active Ingredients

For Ages 12 & Over

Adult

Tussin DM Nighttime Max

Dextromethorphan HBr

Cough Suppressant

Doxylamine Succinate

Antihistamine

Berry Menthol Flavor

• Controls Cough

• Relieves Runny Nose & Sneezing

SEE NEW DOSING

4 FL OZ (118 mL)